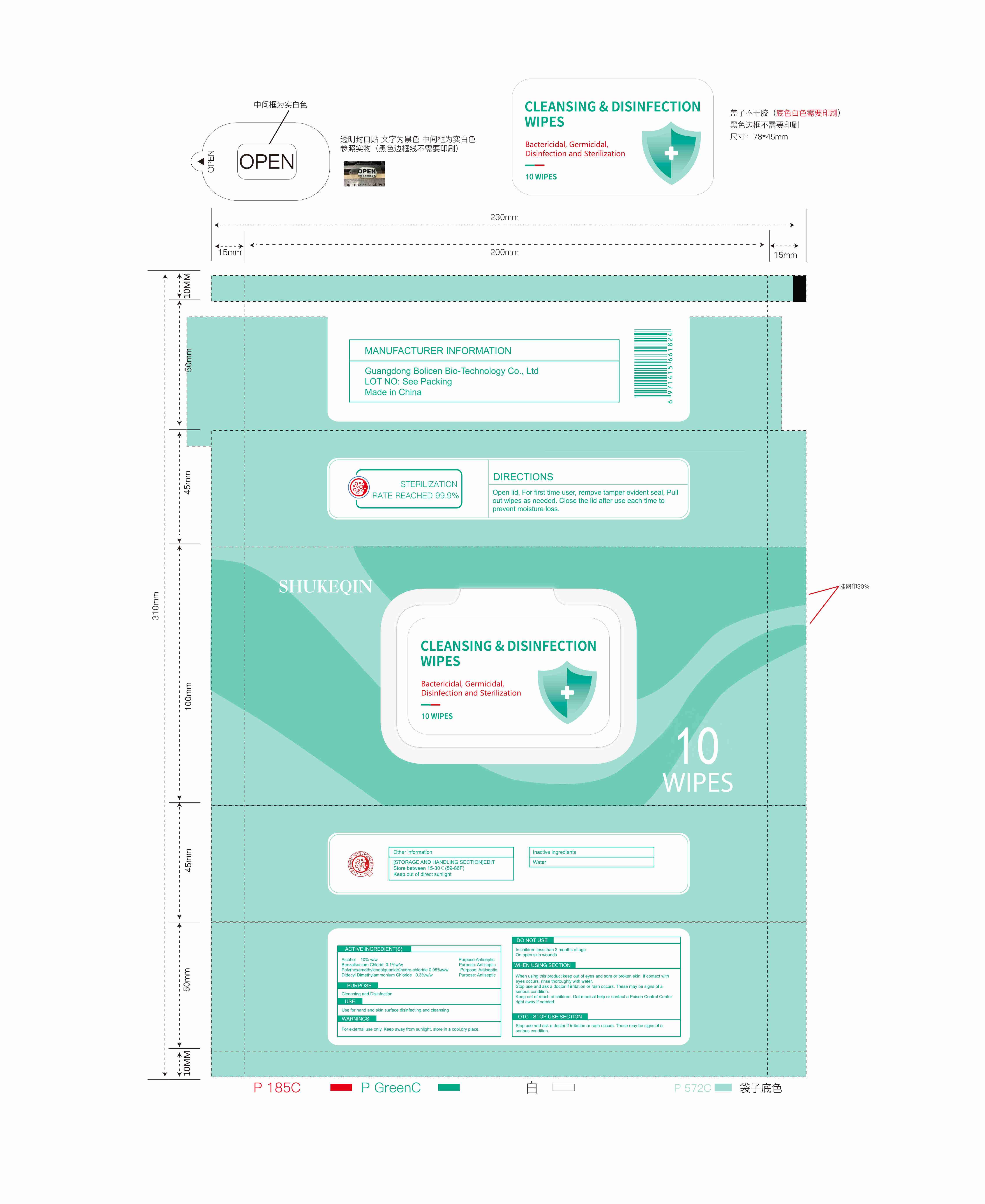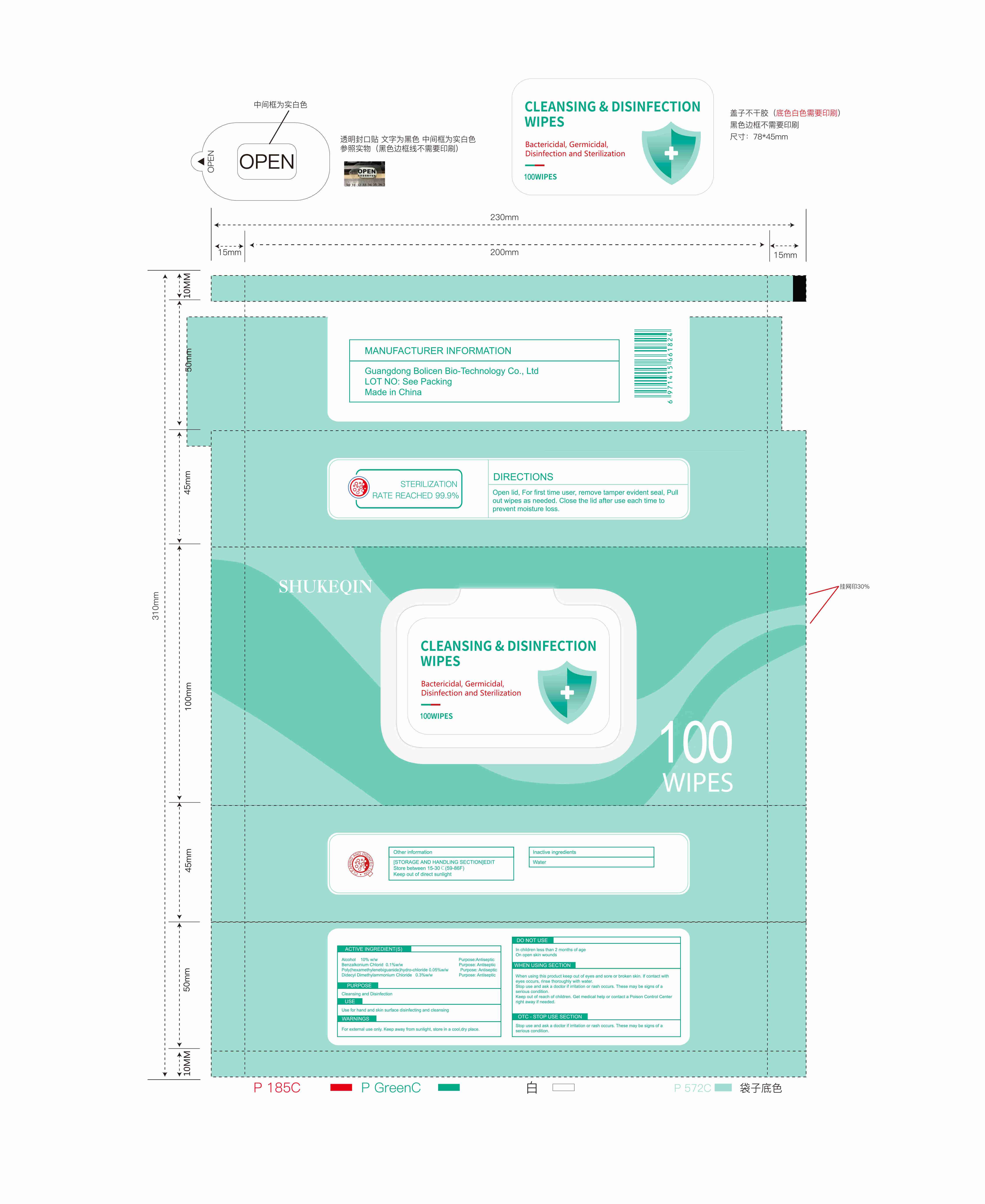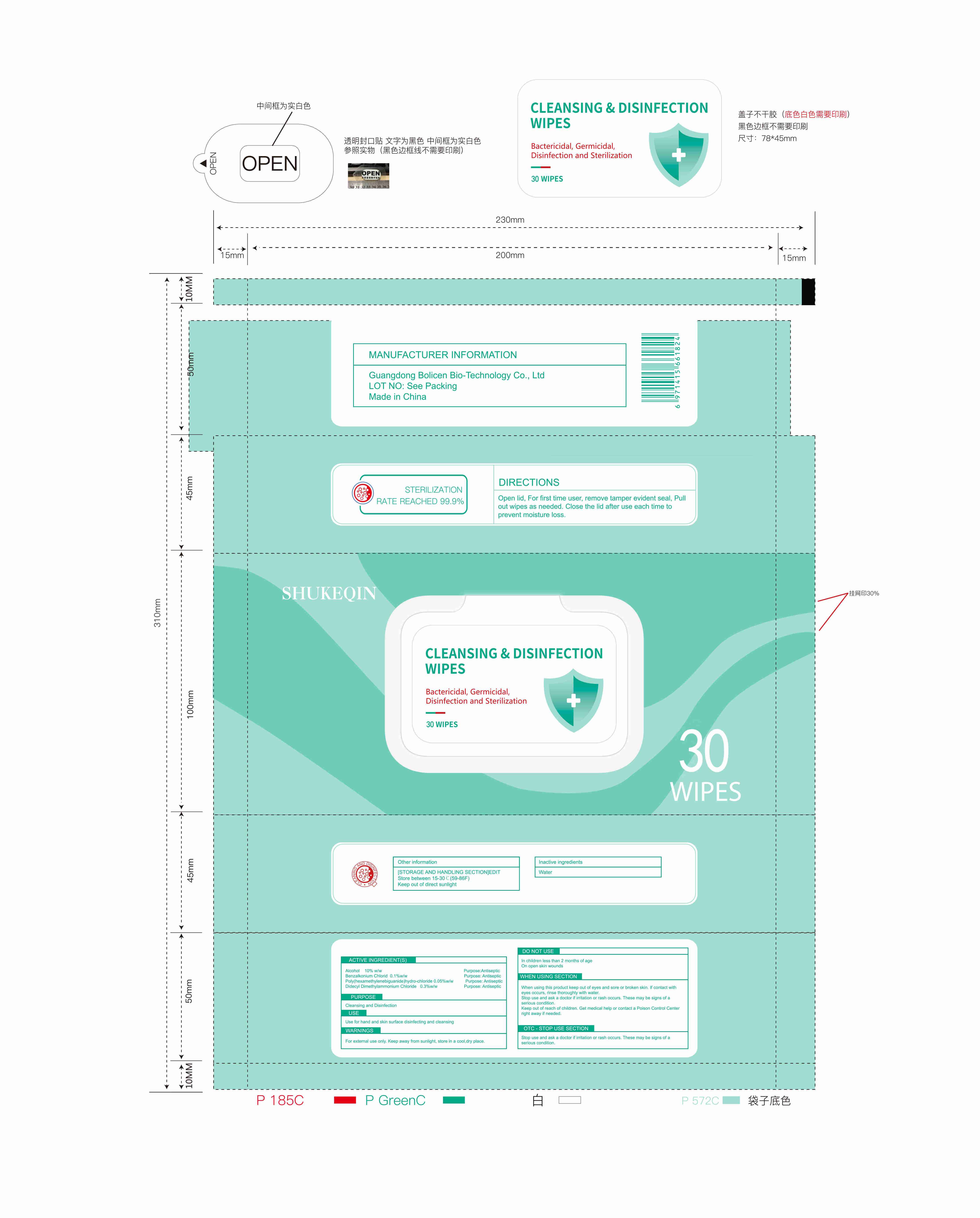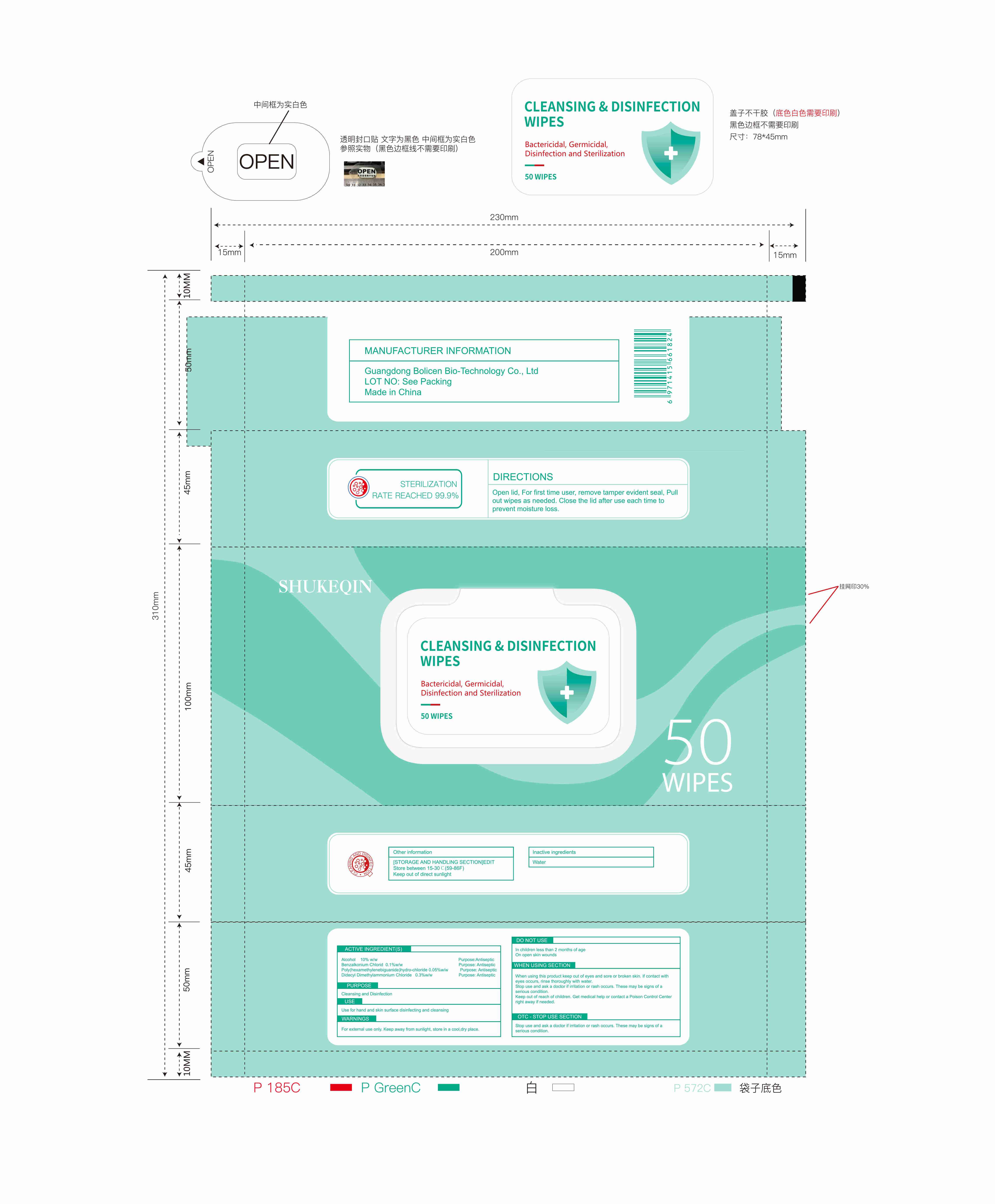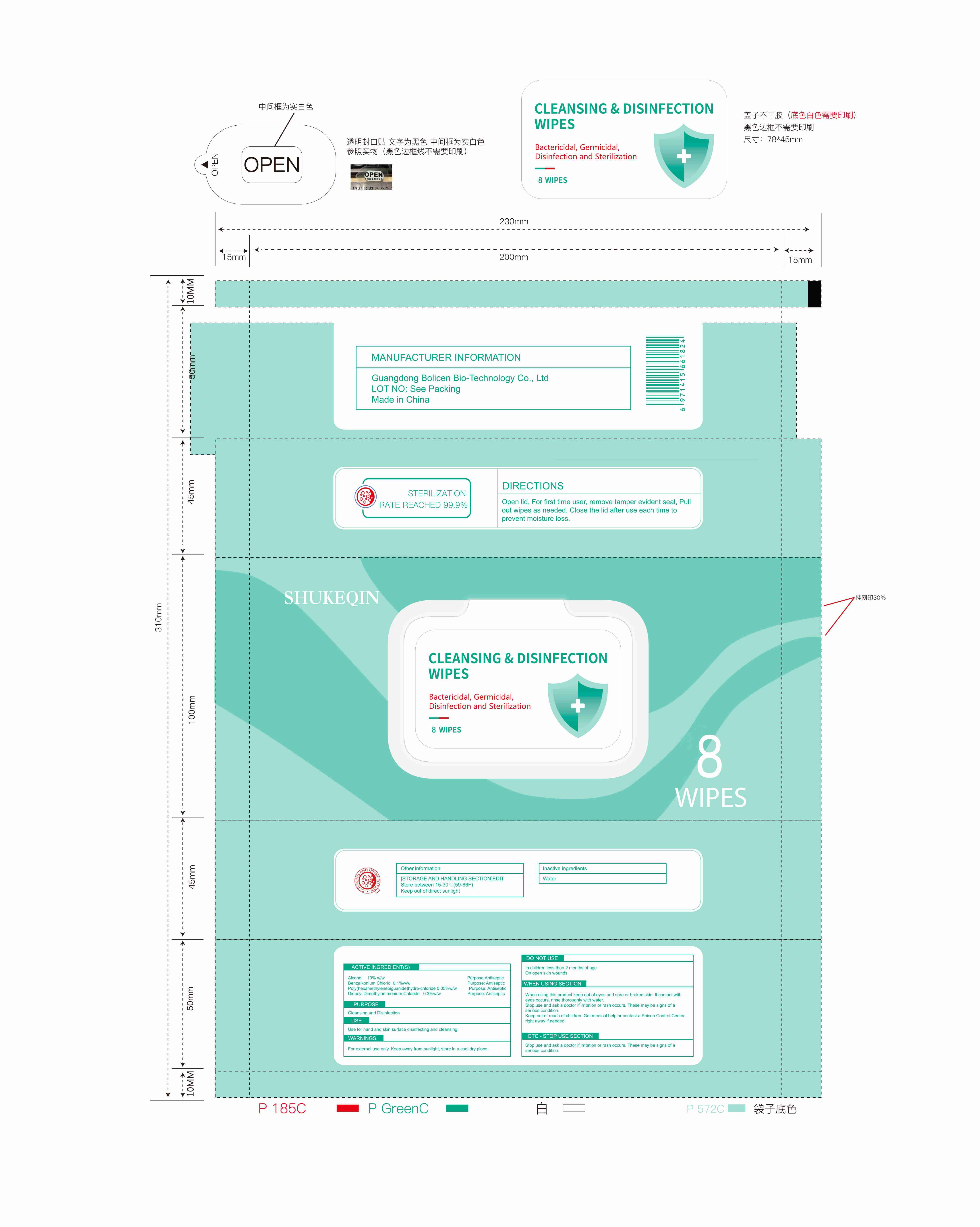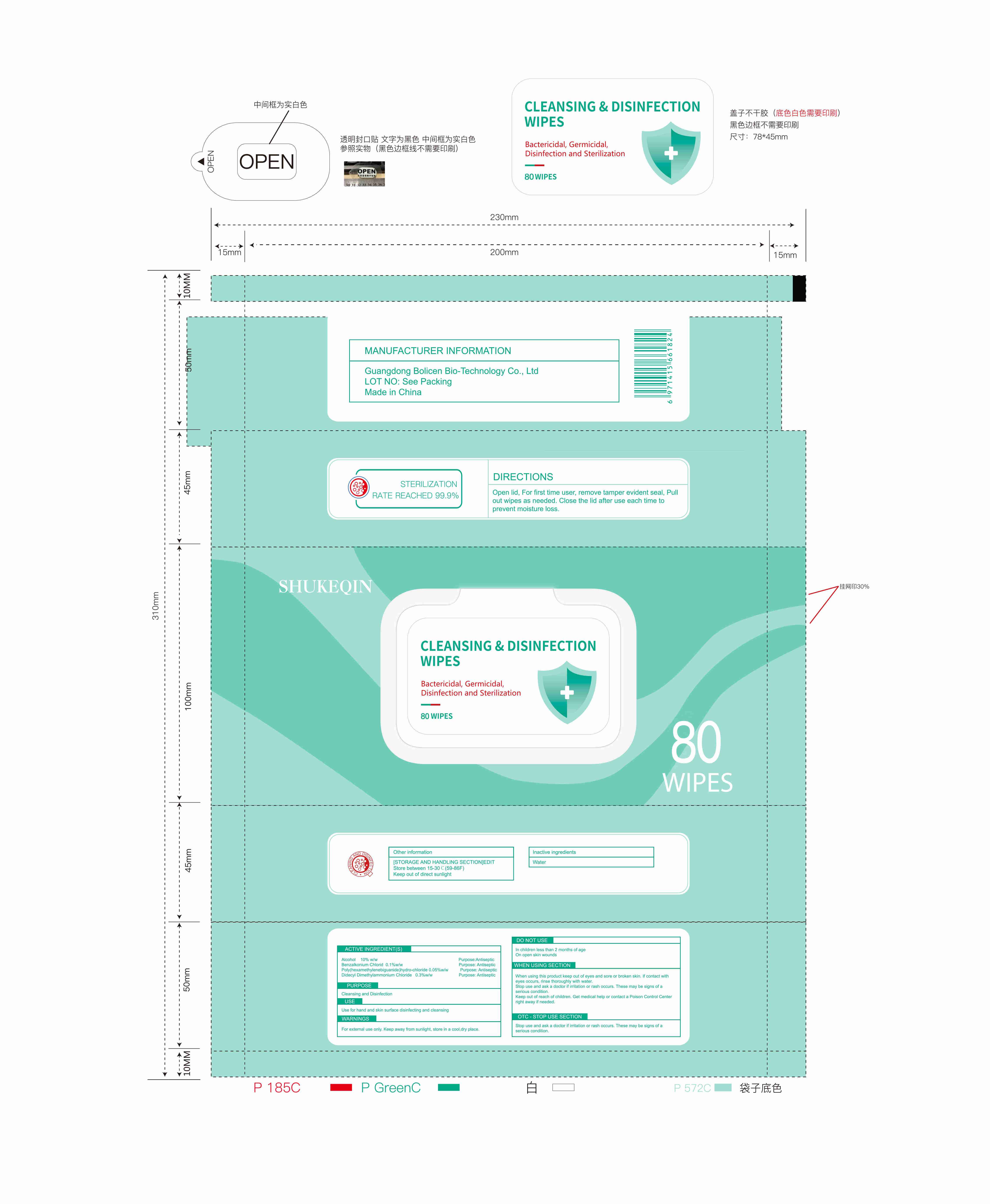 DRUG LABEL: CLEANSING DISINFECTION WIPES
NDC: 78293-008 | Form: CLOTH
Manufacturer: Guangdong Bolicen Bio-Technology Co., Ltd.
Category: otc | Type: HUMAN OTC DRUG LABEL
Date: 20200711

ACTIVE INGREDIENTS: BENZALKONIUM CHLORIDE 0.1 1/100 1; POLIHEXANIDE 0.05 1/100 1; ALCOHOL 10 1/100 1; DIDECYLDIMONIUM CHLORIDE 0.3 1/100 1
INACTIVE INGREDIENTS: WATER

CLEANSING&DISINFECTION WIPES

Active Ingredient(s)

Alcohol 10% w/w

Benzalkonium Chlorid 0. 1%w/w

Poly(hexamethylenebiguanide)hydro-chloride 0.05%w/w

Didecyl Dimethylammonium Chloride 0.3%w/w

Purpose

Antiseptic

Use

USE FOR HAND AND SKIN SURFACE DISINFECTING AND CLEANSING

Warnings

For extemal use only. Keep away from sunlight, store in a cool, dry place

Do not use

In children less than 2 months of age
On open skin wounds

When using this product keep out of eyes and sore or broken skin, If contact with eyes occurs, rinse thoroughly with water.top use and ask a doctor if irritation or rash occurs, These may be signs of a serious condition Keep out of reach of children. Get medical help or contact a Poison Control Center right away if needed

Stop use and ask a doctor if imitation or rash occurs, These may be signs of a serious condition

Keep out of reach of children. Get medical help or contact a Poison Control Center right away if needed

Directions

Open lid, For first time user, remove tamper evident seal, Pullout wipes as needed. Close the lid after use each time top revent moisture loss

Other information

Do not store above 40 °C. May discolor some fabrics and surfaces
Store between15-30°C

Inactive ingredients

Water